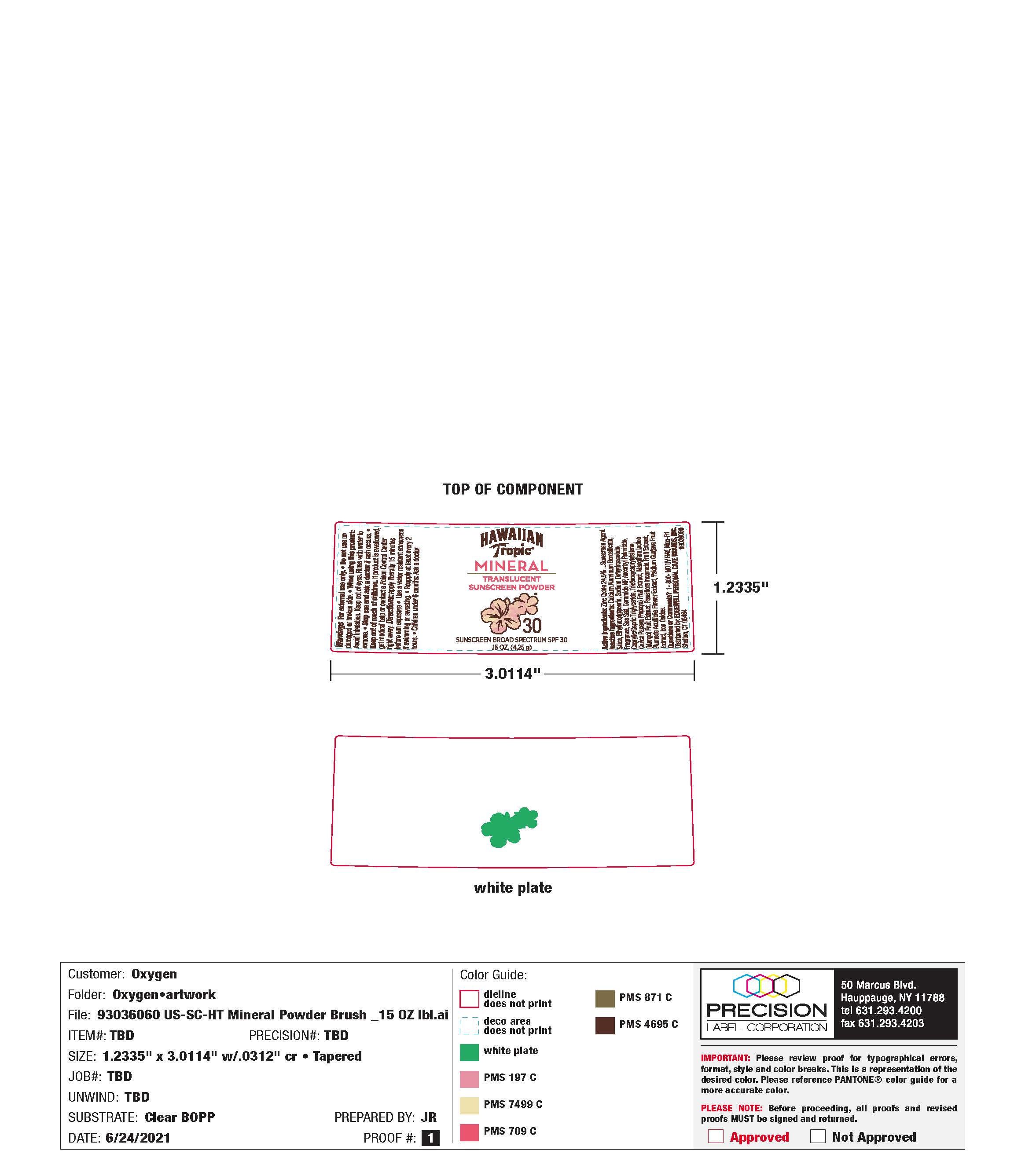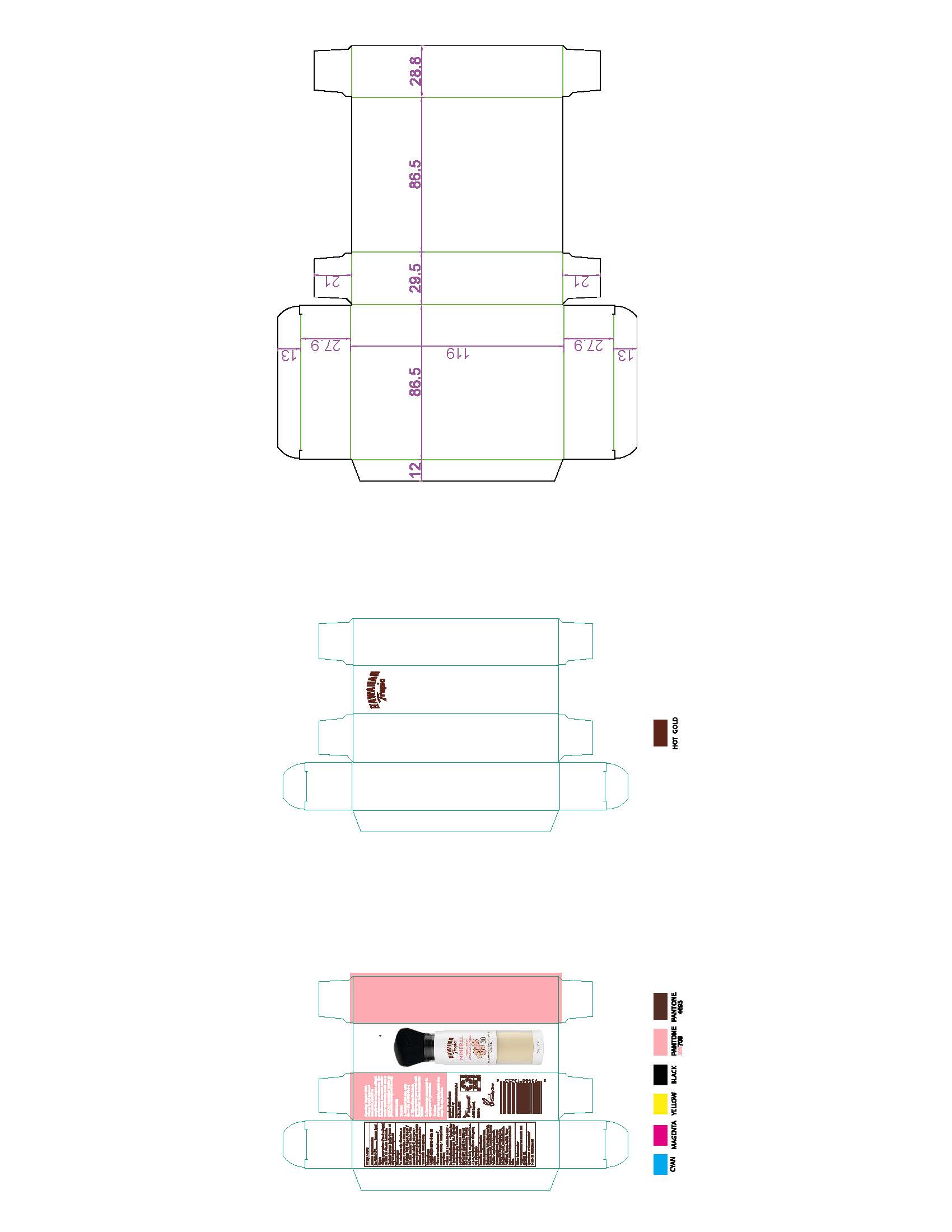 DRUG LABEL: Powder
NDC: 61354-017 | Form: POWDER
Manufacturer: Oxygen Development LLC
Category: otc | Type: HUMAN OTC DRUG LABEL
Date: 20230210

ACTIVE INGREDIENTS: ZINC OXIDE 24.5 g/100 g
INACTIVE INGREDIENTS: CALCIUM ALUMINUM BOROSILICATE 48.26 g/100 g; SILICON DIOXIDE 25 g/100 g; ETHYLHEXYLGLYCERIN 0.5 g/100 g; SODIUM DEHYDROACETATE 0.5 g/100 g

Hawaiian Tropic mineral translucent powder sunscreen broad spectrum SPF 30

Active Ingredient

Zinc oxide 24.5%

Sunscreen Agent

Uses

Helps prevent sunburn

If used as directed with other sun protection measures (see Directions), decreases the risk of cancer and early skin aging caused by the sun

Warnings

For external use only.

Do not use on damage or broken skin.

When using this product: Avoid inhalation.

Keep out of eyes. Rinse with water to remove.

Stop use and ask a doctor if rash occurs.

Keep out of reach of children.

if product is swallowed, get medical help or contact a Poison Control Center right away.

Directions

Apply liberally 15 minutes before sun exposure

Use a water resistant sunscreen if swimming or sweating. Reapply at least every 2 hours.

Children under 6 months: Ask a docstor

Sun Protection Measures. Spendign time in the sun increases your risk of skin cancer and early skin aging. To decrease this risk, regulary use a sunscreen with a Board Spectrum SPF value of 15 or higher and other sun protection measures including limit time in the sun, especially from 10 a.m - 2 p.m, wear long-sleeved shirts, pants, hats, and sunglasses

Inactive Ingredients:

Calcium Aluminunm Borosilicate, Silica, Ethylhexylglycerin, Sodium Dehydroacetate, Fragrance, Sea Salt, Ceramide NP, Ascorbyl Palmitate, Caprylic/Capric Triglyceride, Triethoxycaprylylsilane, Carica Papaya (Papaya) Fruit Extract, Mangifera Indica (Mango) Fruit Extract, Passiflora Incarnata Fruit Extract, Plumeria Acutifolia Flower Extrat, Psidium Guajava Fruit Extract, Iron Oxides

Other information

Protect this product from excessive heat and direct sun